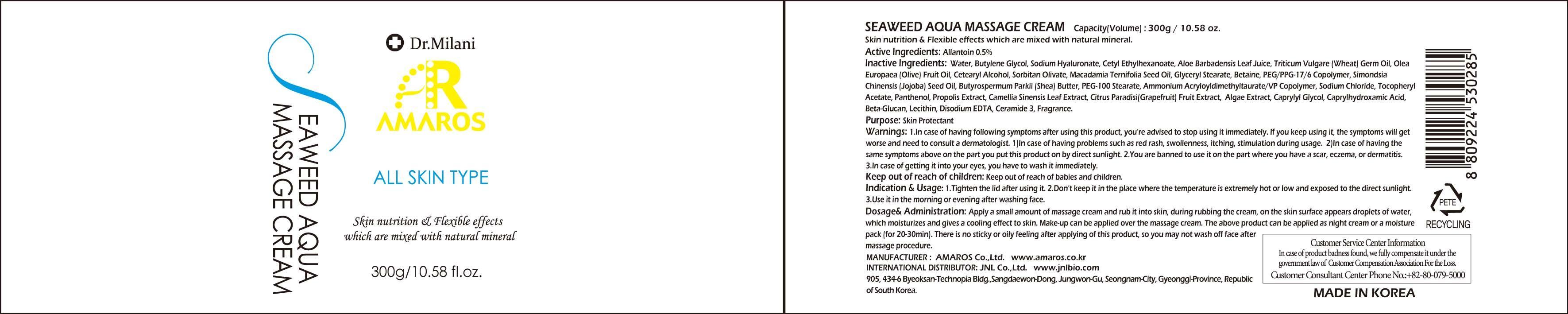 DRUG LABEL: Seaweed Aqua Massage
NDC: 60899-010 | Form: CREAM
Manufacturer: AMAROS CO., LTD.
Category: otc | Type: HUMAN OTC DRUG LABEL
Date: 20190411

ACTIVE INGREDIENTS: Allantoin 1.5 g/300 g
INACTIVE INGREDIENTS: Water; Butylene Glycol

ACTIVE INGREDIENT

Active Ingredient: Allantoin 0.5%

INACTIVE INGREDIENT

Inactive Ingredients: Water, Butylene Glycol, Sodium Hyaluronate, Cetyl Ethylhexanoate, Aloe Barbadensis Leaf Juice, Triticum Vulgare (Wheat) Germ Oil, Olea Europaea (Olive) Fruit Oil, Cetearyl Alcohol, Sorbitan Olivate, Macadamia Ternifolia Seed Oil, Glyceryl Stearate, Betaine, PEG/PPG-17/6 Copolymer, Simondsia Chinensis (Jojoba) Seed Oil, Butyrospermum Parkii (Shea) Butter, PEG-100 Stearate, Ammonium Acryloyldimethyltaurate/VP Copolymer, Sodium Chloride, Tocopheryl Acetate, Panthenol, Propolis Extract, Camellia Sinensis Leaf Extract, Citrus Paradisi (Grapefruit) Fruit Extract, Algae Extract, Caprylyl Glycol, Caprylhydroxamic Acid, Beta-Glucan, Lecithin, Disodium EDTA, Ceramide 3, Fragrance.

PURPOSE

Purpose: Skin Protectant

WARNINGS

Warnings: 1. In case of having following symptoms after using this product, you're advised to stop using it immediately. If you keep using it, the symptoms will get worse and need to consult a dermatologist. 1) In case of having problems such as red rash, swollenness, itching, stimulation during usage. 2) In case of having the same symptoms above on the part you put this product on by direct sunlight. 2. You are banned to use it on the part where you have a scar, eczema, or dermatitis. 3. In case of getting it into your eyes, you have to wash it immediately.

Keep out of reach of children: Keep out of reach of babies and children.

INDICATIONS AND USAGE

Indication and Usage: 1. Tighten the lid after using it. 2. Don't keep it in the place where the temperature is extremely hot or low and exposed to the direct sunlight. 3. Use it in the morning or evening after washing face.

Dosage and Administration: Apply a small amount of massage cream and rub it into skin, during rubbing the cream, on the skin surface appears droplets of water, which moisturizes and gives a cooling effect to skin. Make-up can be applied over the massage cream. The above product can be applied as night cream or a moisture pack (for 20-30min). There is no sticky or oily feeling after applying of this product, so you may not wash off face after massage procedure.